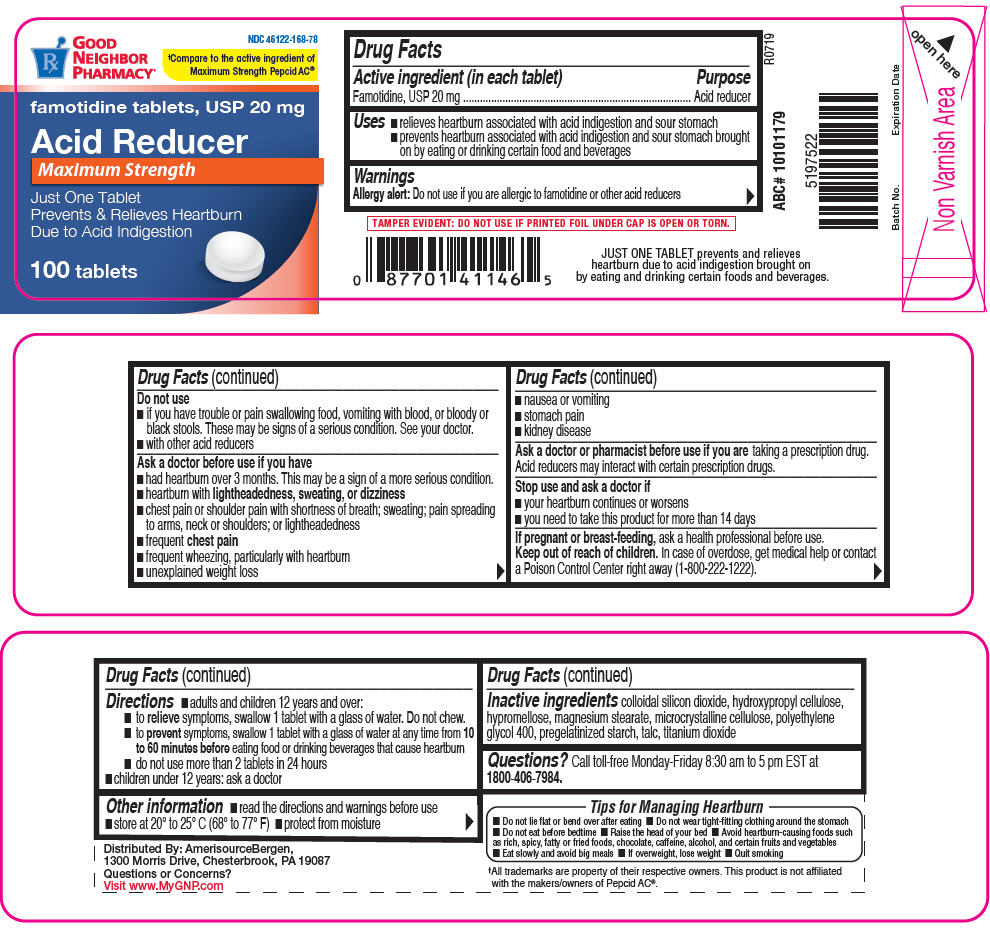 DRUG LABEL: Famotidine
NDC: 46122-168 | Form: TABLET, FILM COATED
Manufacturer: AMERISOURCE BERGEN
Category: otc | Type: HUMAN OTC DRUG LABEL
Date: 20190722

ACTIVE INGREDIENTS: FAMOTIDINE 20 mg/1 1
INACTIVE INGREDIENTS: SILICON DIOXIDE; HYDROXYPROPYL CELLULOSE (1600000 WAMW); HYPROMELLOSE, UNSPECIFIED; MAGNESIUM STEARATE; MICROCRYSTALLINE CELLULOSE; POLYETHYLENE GLYCOL 400; STARCH, CORN; TALC; TITANIUM DIOXIDE

Famotidine

Drug Facts

Active ingredient (in each tablet)

Famotidine, USP 20 mg

Purpose

Acid reducer

Uses

- relieves heartburn associated with acid indigestion and sour stomach
- prevents heartburn associated with acid indigestion and sour stomach brought on by eating or drinking certain food and beverages

Warnings

Allergy alert

Do not use if you are allergic to famotidine or other acid reducers

Do not use

- if you have trouble or pain swallowing food, vomiting with blood, or bloody or black stools. These may be signs of a serious condition. See your doctor.
- with other acid reducers

Ask a doctor before use if you have

- had heartburn over 3 months. This may be a sign of a more serious condition.
- heartburn with lightheadedness, sweating, or dizziness
- chest pain or shoulder pain with shortness of breath; sweating; pain spreading to arms, neck or shoulders; or lightheadedness
- frequent chest pain
- frequent wheezing, particularly with heartburn
- unexplained weight loss
- nausea or vomiting
- stomach pain
- kidney disease

Ask a doctor or pharmacist before use if you are taking a prescription drug. Acid reducers may interact with certain prescription drugs.

Stop use and ask a doctor if

- your heartburn continues or worsens
- you need to take this product for more than 14 days

PREGNANCY OR BREAST FEEDING

If pregnant or breast-feeding, ask a health professional before use.

Keep out of reach of children. In case of overdose, get medical help or contact a Poison Control Center right away (1-800-222-1222).

Directions

- adults and children 12 years and over:
  - to relieve symptoms, swallow 1 tablet with a glass of water. Do not chew.
  - to prevent symptoms, swallow 1 tablet with a glass of water at any time from 10 to 60 minutes before eating food or drinking beverages that cause heartburn
  - do not use more than 2 tablets in 24 hours
- children under 12 years: ask a doctor

Other information

- read the directions and warnings before use
- store at 20° to 25° C (68° to 77° F)
- protect from moisture

Inactive ingredients

colloidal silicon dioxide, hydroxypropyl cellulose, hypromellose, magnesium stearate, microcrystalline cellulose, polyethylene glycol 400, pregelatinized starch, talc, titanium dioxide

Questions?

Call toll-free Monday-Friday 8:30 am to 5 pm EST at 1800-406-7984.

Distributed By: AmerisourceBergen,
1300 Morris Drive, Chesterbrook, PA 19087

PRINCIPAL DISPLAY PANEL - 20 mg Tablet Bottle Label

NDC 46122-168-78

GOOD
NEIGHBOR
PHARMACY®

†Compare to the active ingredient of
Maximum Strength Pepcid AC®

famotidine tablets, USP 20 mg

Acid Reducer

Maximum Strength

Just One Tablet
Prevents & Relieves Heartburn
Due to Acid Indigestion

100 tablets